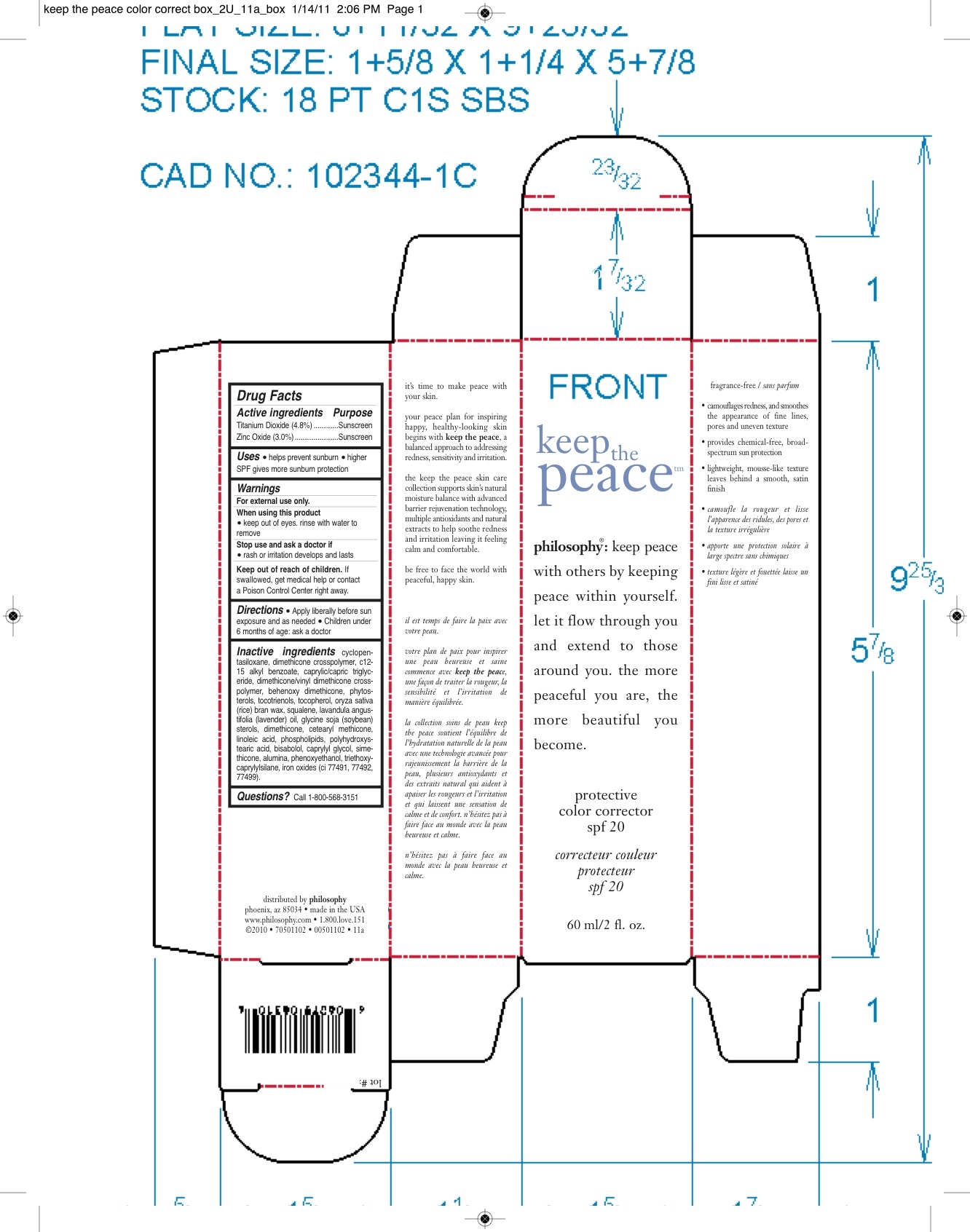 DRUG LABEL: Keep The Peace Protect and Correct
NDC: 50184-6600 | Form: CREAM
Manufacturer: Philosophy, Inc.
Category: otc | Type: HUMAN OTC DRUG LABEL
Date: 20110124

ACTIVE INGREDIENTS: TITANIUM DIOXIDE 2.88 mL/60 mL; ZINC OXIDE 1.8 mL/60 mL
INACTIVE INGREDIENTS: CYCLOMETHICONE 5; DIMETHICONE; ALKYL (C12-15) BENZOATE; MEDIUM-CHAIN TRIGLYCERIDES; ALPHA-TOCOPHEROL; RICE BRAN; SQUALENE; ENGLISH LAVENDER OIL; SOYBEAN; DIMETHICONE; LINOLEIC ACID; EGG PHOSPHOLIPIDS; LEVOMENOL; CAPRYLYL GLYCOL; ALUMINUM OXIDE; PHENOXYETHANOL; OCTYLTRIETHOXYSILANE; FERROSOFERRIC OXIDE; FERRIC OXIDE RED; FERRIC OXIDE YELLOW

DRUG FACTS

ACTIVE INGREDIENT

TITANIUM DIOXIDE......4.8%

ZINC OXIDE..........3.0%

INACTIVE INGREDIENT

CYCLOPENTASILOXANE, DIMETHICONE CROSSPOLYMER, C12-15 ALKYL BENZOATE, CAPRYLIC/CAPRIC TRIGLYCERIDE, DIMETHICONE/VINYL DIMETHICONE CROSSPOLYMER, BEHENOXY DIMETHICONE, PHYTOSTEROLS, TOCOTRIENOLS, TOCOPHEROL, ORYZA SATIVA (RICE) BRAN WAX, SQUALENE, LAVANDULA ANGUSTIFOLIA (LAVENDER) OIL, GLYCINE SOJA (SOYBEAN) STEROLS, DIMETHICONE, CETEARYL METHICONE, LINOLEIC ACID, PHOSPHOLIPIDS, POLYHYDROXYSTEARIC ACID, BISABOLOL, CAPYLYL GLYCOL, SIMETHICONE, ALUMINA, PHENOXYETHANOL, TRIETHOXYCAPRYLYLSILANE, IRON OXIDES (CI 77491, 77492, 77499).

PURPOSE

Sunscreen

Uses: helps prevent suburn

higher SPF gives more sunburn protection

WARNINGS

FOR EXTERNAL USE ONLY.

WHEN USING THIS PRODUCT.

KEEP OUT OF EYES. RINSE WITH WATER TO REMOVE

STOP USE AND ASK DOCTOR IF A RASH OR IRRITATION DEVELOPS AND LASTS.

KEEP OUT OF REACH OF CHILDREN.

IF SWALLOWED, GET MEDICAL HELP OR CONTACT A POISON CONTROL CENTER RIGHT AWAY.

QUESTIONS? CALL - 1-800-568-3515